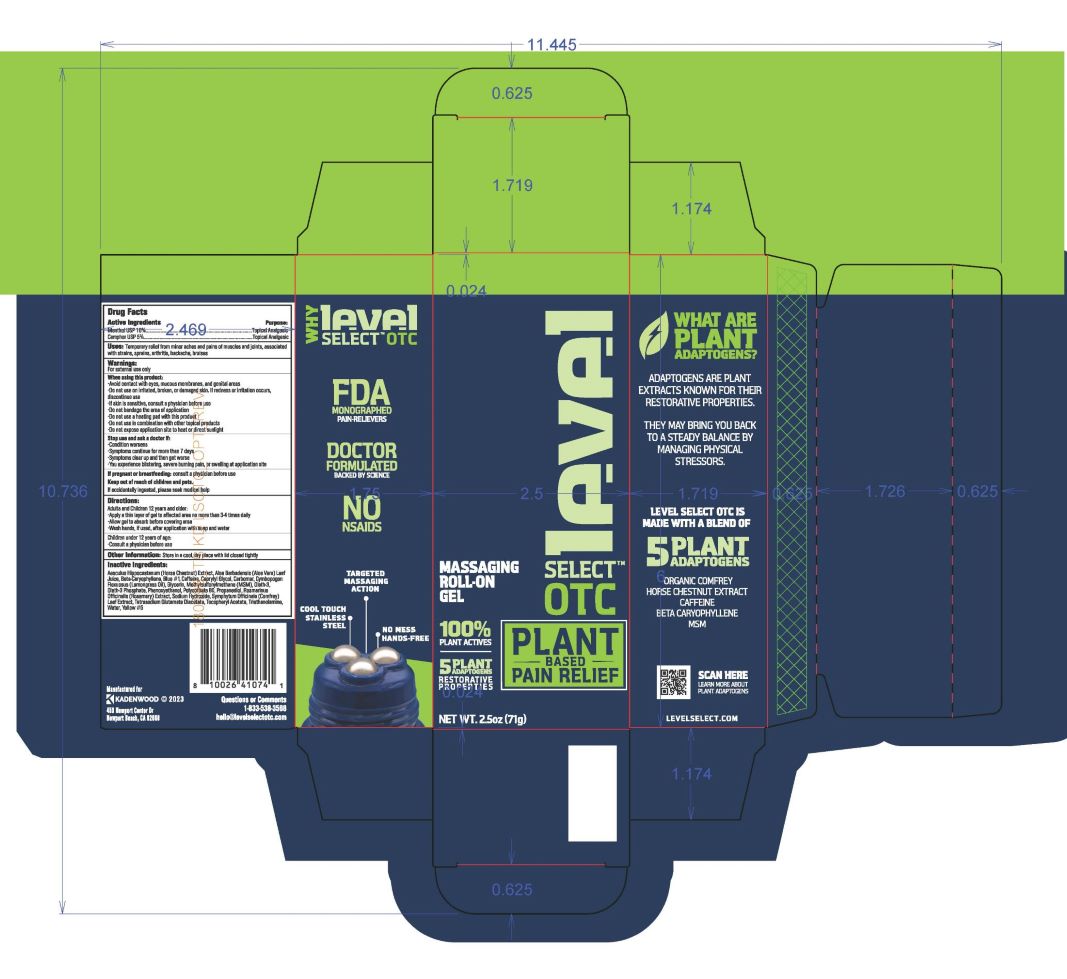 DRUG LABEL: Level Select Menthol Camphor Roll On
NDC: 83191-003 | Form: GEL
Manufacturer: Kandenwood LLC
Category: otc | Type: HUMAN OTC DRUG LABEL
Date: 20241228

ACTIVE INGREDIENTS: MENTHOL 10 g/100 g; CAMPHOR (SYNTHETIC) 5 g/100 g
INACTIVE INGREDIENTS: OLETH-3; OLETH-3 PHOSPHATE; PROPANEDIOL; TROLAMINE; FD&C YELLOW NO. 5; WATER; POLYSORBATE 80; SODIUM HYDROXIDE; TETRASODIUM GLUTAMATE DIACETATE; FD&C BLUE NO. 1; CAPRYLYL GLYCOL; ALOE VERA LEAF; GLYCERIN; CYMBOPOGON FLEXUOSUS LEAF; CAFFEINE; HORSE CHESTNUT; ROSEMARY OIL; DIMETHYL SULFONE; COMFREY; CARYOPHYLLENE; CARBOMER COPOLYMER TYPE A; PHENOXYETHANOL

Level Select 10% Menthol, 5% Camphor 2.5 oz Roll On Tube

OTC-ACTIVE INGREDIENTS

Menthol 10%

Camphor 5%

OTC-PURPOSE

Topical Analgesic

Uses

Temporary relief from minor aches and pains of muscles and joints, associated with strains, sprains,arthritis, backache, bruises

Warnings

For external use only

When using this product:

- Avoid contact with eyes, mucous membranes, and genital areas.
- Do not use on irritated, broken, or damaged skin. If redness or irritation occurs, discontinue use
- If skin is sensitive, consult a physician before use
- Do not bandage the area of application
- Do not use a heating pad with this product
- Do not use in combination with other topical products
- Do not expose appliation site to heat or direct sunlight

Stop use and ask a doctor if:

- Condition worsens
- Symptoms continue for more than 7 days
- Symptoms clear up and then get worse
- You experience blistering, severe burning pain, or swelling at applicaton site

If pregnant or breastfeeding:

consult a physician before use

Keep out of reach of chlidren and pets

If accidentally ingested, please seek medical help

Directions:

Adults and Children 12 years and older:

- Apply a thin layer of gel to affected area no more than 3-4 times daily
- Allow gel to absorb before covering area
- Wash hands, if used, after appliation with soap and water

_______________________________________________________________

Children under 12 years of age:

- Consult a physician before use

Other Information:

Store in a cool, dry place iwth lid closed tightly

Inactive Ingredients:

Aesculus Hippocastanum (Horse Chestnut) Extract, Aloe Barbadensis (Aloe Vera) Leaf Juice, Beta-Caryophyllene, Blue #1, Caffeine, Caprylyl Glycol, Carbomer, Cymbopogon, Flexuosus (Lemongrass Oil), Glycerin, Methylsulfonylmethane (MSM), Oleth-3, Oleth-3 Phosphate, Phenoxyethanol, Polysorbate 80, Propanediol, Rosmarinus Officinalis (Rosemary) Extract, Sodium Hydroxide, Symphytum Offcinate (Comfrey) Leaf Extract, Tetrasodium Glutamate Diacetate, Tocopheryl Acetate (Vitamin E) Triethanolamine, Water, Yellow #5